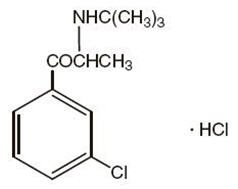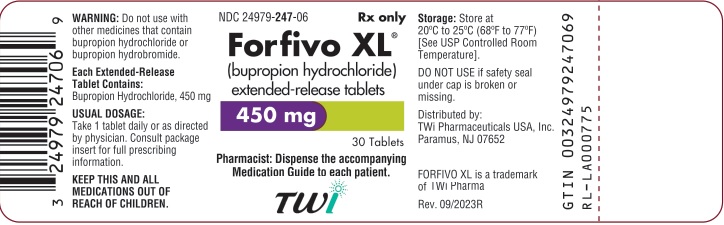 DRUG LABEL: Forfivo 
NDC: 24979-247 | Form: TABLET, FILM COATED, EXTENDED RELEASE
Manufacturer: Upsher-Smith Laboratories, LLC
Category: prescription | Type: HUMAN PRESCRIPTION DRUG LABEL
Date: 20251106

ACTIVE INGREDIENTS: BUPROPION HYDROCHLORIDE 450 mg/1 1
INACTIVE INGREDIENTS: HYDROXYPROPYL CELLULOSE (1600000 WAMW); HYDROCHLORIC ACID; STEARIC ACID; SILICON DIOXIDE; MAGNESIUM STEARATE; HYPROMELLOSE, UNSPECIFIED; TRIACETIN; TALC; METHACRYLIC ACID AND ETHYL ACRYLATE COPOLYMER; POLYETHYLENE GLYCOL 8000; TITANIUM DIOXIDE; CARBOXYMETHYLCELLULOSE SODIUM, UNSPECIFIED; POLYETHYLENE OXIDE 2000000; POLYVINYL ACETATE; POVIDONE K30

HIGHLIGHTS OF PRESCRIBING INFORMATION

These highlights do not include all the information needed to use FORFIVO XL safely and effectively. See full prescribing information for FORFIVO XL.
FORFIVO XL (bupropion hydrochloride) extended-release tablets, for oral use
Initial U.S. Approval: 1985

WARNING: SUICIDAL THOUGHTS AND BEHAVIORS

See full prescribing information for complete boxed warning

•Increased risk of suicidal thinking and behavior in children, adolescents, and young adults taking antidepressants (5.1).

•Monitor for worsening and emergence of suicidal thoughts and behaviors (5.1).

1 INDICATIONS AND USAGE

FORFIVO XL is an aminoketone antidepressant indicated for the treatment of major depressive disorder (MDD) (1). The efficacy was established in two 4-week trials, one 6-week trial with bupropion immediate-release formulation, and one maintenance trial with bupropion sustained-release formulation, all in adults (14). Periodically re-evaluate long-term usefulness for the individual patient (1).

2 DOSAGE AND ADMINISTRATION

1. Use one tablet (450 mg) once daily without regard to food (2.1).
2. Swallow the tablet whole. Do not chew, divide, or crush (2.1).
3. Do not initiate treatment with FORFIVO XL. Use another bupropion formulation for initial dose titration (2.2).
4. Can be used in patients who are receiving 300 mg/day of another bupropion formulation for at least 2 weeks, and require a dosage of 450 mg/day (2.2).
5. Patients who are currently being treated with other bupropion products at 450 mg/day can be switched to equivalent dose of FORFIVO XL once daily (2.2).

3 DOSAGE FORMS AND STRENGTHS

•Extended-release tablets: 450 mg (3)

4 CONTRAINDICATIONS

•Seizure disorder (4, 5.3)

•Current use of other bupropion products (4, 5.3)

•Current or prior diagnosis of bulimia or anorexia nervosa (4, 5.3)

•Abrupt discontinuation of alcohol, benzodiazepines, barbiturates, or antiepileptic drugs (4, 5.3)

•Monoamine Oxidase Inhibitors (MAOIs): Do not use MAOIs intended to treat psychiatric disorders with FORFIVO XL or within 14 days of stopping treatment with FORFIVO XL. Do not use FORFIVO XL within 14 days of stopping an MAOI intended to treat psychiatric disorders. In addition, do not start FORFIVO XL in a patient who is being treated with linezolid or intravenous methylene blue (4, 7.6).

•Known hypersensitivity to bupropion or other ingredients of FORFIVO XL (4, 5.8)

5 WARNINGS AND PRECAUTIONS

- Neuropsychiatric Adverse Events During Smoking Cessation: Postmarketing reports of serious or clinically significant neuropsychiatric adverse events have included changes in mood (including depression and mania), psychosis, hallucinations, paranoia, delusions, homicidal ideation, aggression, hostility, agitation, anxiety, and panic, as well as suicidal ideation, suicide attempt, and completed suicide. Observe patients attempting to quit smoking with FORFIVO XL for the occurrence of such symptoms and instruct them to discontinue FORFIVO XL and contact a healthcare provider if they experience such adverse events (5.2).
- Seizure Risk: The risk is dose dependent. Discontinue if seizure occurs (4, 5.3, 7.3).
- Hypertension: FORFIVO XL can increase blood pressure. Monitor blood pressure before initiating treatment and periodically during treatment (5.4).
- Activation of Mania/Hypomania: Screen patients for bipolar disorder and monitor for these symptoms (5.5).
- Psychosis and Other Neuropsychiatric Reactions: Discontinue if such reactions occur (5.6).
- Angle-closure Glaucoma: Angle-closure glaucoma has occurred in patients with untreated anatomically narrow angles treated with antidepressants (5.7).

6 ADVERSE REACTIONS

Most common adverse reactions are (incidence ≥ 5%; ≥ 2 times placebo rate): dry mouth, nausea, insomnia, dizziness, pharyngitis, abdominal pain, agitation, anxiety, tremor, palpitation, sweating, tinnitus, myalgia, anorexia, urinary frequency, rash (6.1)

To report SUSPECTED ADVERSE REACTIONS, contact TWi Pharmaceuticals, Inc. at 1-844-518-2989 or FDA at 1-800-FDA-1088 or www.fda.gov/medwatch.

7 DRUG INTERACTIONS

1. CYP2B6 Inhibitors: Ticlopidine or clopidogrel may increase bupropion exposure. Coadministration of FORFIVO XL with ticlopidine or clopidogrel is not recommended (7.1).
2. CYP2B6 Inducers: Dose increase may be necessary if coadministered with CYP2B6 inducers (e.g., ritonavir, lopinavir, efavirenz, carbamazepine, phenobarbital, and phenytoin) based on clinical exposure, but should not exceed the maximum recommended dose (7.1).
3. Drugs Metabolized by CYP2D6: Bupropion inhibits CYP2D6 and can increase concentrations of: antidepressants (e.g., venlafaxine, nortriptyline, imipramine, desipramine, paroxetine, fluoxetine, sertraline), antipsychotics (e.g., haloperidol, risperidone, thioridazine), beta-blockers (e.g., metoprolol), and Type 1C antiarrhythmics (e.g., propafenone, flecainide). Consider dose reduction when using with bupropion (7.2).
4. Drugs That Lower Seizure Threshold: Dose FORFIVO XL with extreme caution (5.3, 7.3).
5. Dopaminergic Drugs (levodopa and amantadine): CNS toxicity can occur when used concomitantly with FORFIVO XL (7.4).
6. MAOIs: Increased risk of hypertensive reactions can occur when used concomitantly with FORFIVO XL (7.6).
7. Drug-Laboratory Test Interactions: FORFIVO XL can cause false-positive urine test results for amphetamines (7.7).

8 USE IN SPECIFIC POPULATIONS

1. Renal Impairment: Because there is no lower dose strength for FORFIVO XL, FORFIVO XL is not recommended in patients with renal impairment (8.6).
2. Hepatic Impairment: Because there is no lower dose strength for FORFIVO XL, FORFIVO XL is not recommended in patients with hepatic impairment (8.7).

FULL PRESCRIBING INFORMATION

WARNING: SUICIDAL THOUGHTS AND BEHAVIORS

SUICIDALITY AND ANTIDEPRESSANT DRUGS

Antidepressants increased the risk of suicidal thoughts and behavior in children, adolescents, and young adults in short‑term trials. These trials did not show an increase in the risk of suicidal thoughts and behavior with antidepressant use in subjects over age 24; there was a reduction in risk with antidepressant use in subjects aged 65 and older [see Warnings and Precautions (5.1)].

In patients of all ages who are started on antidepressant therapy, monitor closely for worsening and for emergence of suicidal thoughts and behaviors. Advise families and caregivers of the need for close observation and communication with the prescriber. FORFIVO XL is not approved for use in pediatric patients [see Warnings and Precautions (5.1)].

1 INDICATIONS AND USAGE

FORFIVO XL (bupropion hydrochloride extended-release tablets) is indicated for the treatment of major depressive disorder (MDD), as defined by the Diagnostic and Statistical Manual (DSM).

The efficacy of the immediate-release formulation of bupropion was established in two 4-week controlled inpatient trials and one 6-week controlled outpatient trial of adult patients with MDD. The efficacy of the sustained-release formulation of bupropion in the maintenance treatment of MDD was established in a long-term (up to 44 weeks), placebo-controlled trial in patients who had responded to bupropion in an 8-week study of acute treatment [see Clinical Studies (14)].

The physician who elects to use FORFIVO XL for extended periods should periodically reevaluate the long-term usefulness of the drug for the individual patient.

2 DOSAGE AND ADMINISTRATION

2.1 General Instructions for Use

One tablet (450 mg) of FORFIVO XL should be taken once daily without regard to meals. FORFIVO XL should be swallowed whole and not crushed, divided, or chewed.

2.2 Initial Treatment with FORFIVO XL

Do not initiate treatment with FORFIVO XL because the 450 mg tablet is the only available dose formulation. Use another bupropion formulation for initial dose titration (referring to prescribing information of other bupropion products).

FORFIVO XL can be used in patients who are receiving 300 mg/day of another bupropion formulation for at least 2 weeks, and require a dosage of 450 mg/day.

Patients who are currently being treated with other bupropion products at 450 mg/day can be switched to an equivalent dose of FORFIVO XL once daily.

2.3 Maintenance Treatment with FORFIVO XL

It is generally agreed that acute episodes of depression require several months or longer of sustained antidepressant treatment beyond the response in the acute episode. It is unknown whether the 450 mg dose needed for maintenance treatment is identical to the dose that provided an initial response. Periodically reassess the need for maintenance treatment and the appropriate dose for such treatment.

2.4 To Discontinue FORFIVO XL, Taper the Dose

Because the 450 mg tablet is the only available dose formulation, use another bupropion formulation for tapering the dose prior to discontinuation (referring to prescribing information of other bupropion products).

2.5 Patients with Impaired Hepatic Function

Because there is no lower dose strength for FORFIVO XL, FORFIVO XL is not recommended in patients with hepatic impairment [see Use in Specific Populations (8.7) and Clinical Pharmacology (12.3)].

2.6 Patients with Impaired Renal Function

Because there is no lower dose strength for FORFIVO XL, FORFIVO XL is not recommended in patients with renal impairment [see Use in Specific Populations (8.6) and Clinical Pharmacology (12.3)].

2.7 Switching a Patient To or From a Monoamine Oxidase Inhibitor (MAOI) Antidepressant

At least 14 days should elapse between discontinuation of an MAOI intended to treat depression and initiation of therapy with FORFIVO XL. Conversely, at least 14 days should be allowed after stopping FORFIVO XL before starting an MAOI antidepressant [see Contraindications (4) and Drug Interactions (7.6)].

2.8 Use of FORFIVO XL with Reversible MAOIs Such as Linezolid or Methylene Blue

Do not start FORFIVO XL in a patient who is being treated with a reversible MAOI such as linezolid or intravenous methylene blue. Drug interactions can increase the risk of hypertensive reactions. In a patient who requires more urgent treatment of a psychiatric condition, nonpharmacological interventions, including hospitalization, should be considered [see Contraindications (4)].

In some cases, a patient already receiving therapy with FORFIVO XL may require urgent treatment with linezolid or intravenous methylene blue. If acceptable alternatives to linezolid or intravenous methylene blue treatment are not available and the potential benefits of linezolid or intravenous methylene blue treatment are judged to outweigh the risks of hypertensive reactions in a particular patient, FORFIVO XL should be stopped promptly, and linezolid or intravenous methylene blue can be administered. The patient should be monitored for 2 weeks or until 24 hours after the last dose of linezolid or intravenous methylene blue, whichever comes first. Therapy with FORFIVO XL may be resumed 24 hours after the last dose of linezolid or intravenous methylene blue.

The risk of administering methylene blue by nonintravenous routes (such as oral tablets or by local injection) or in intravenous doses much lower than 1 mg/kg with FORFIVO XL is unclear. The clinician should, nevertheless, be aware of the possibility of a drug interaction with such use [see Contraindications (4) and Drug Interactions (7.6)].

3 DOSAGE FORMS AND STRENGTHS

FORFIVO XL Extended-Release Tablets, 450 mg of bupropion hydrochloride, are white to off-white, oblong-shaped tablets with the logo “Forfivo” printed on one side.

4 CONTRAINDICATIONS

1. FORFIVO XL is contraindicated in patients with a seizure disorder [see Warnings and Precautions (5.3)].
2. FORFIVO XL is contraindicated in patients treated currently with other bupropion products because the incidence of seizure is dose dependent [see Warnings and Precautions (5.3)].
3. FORFIVO XL is contraindicated in patients with a current or prior diagnosis of bulimia or anorexia nervosa because a higher incidence of seizures was observed in such patients treated with bupropion [see Warnings and Precautions (5.3)].
4. FORFIVO XL is contraindicated in patients undergoing abrupt discontinuation of alcohol, benzodiazepines, barbiturates, and antiepileptic drugs [see Warnings and Precautions (5.3) and Drug Interactions (7.3)].
5. The use of MAOIs (intended to treat psychiatric disorders) concomitantly with FORFIVO XL or within 14 days of discontinuing treatment with FORFIVO XL is contraindicated. There is an increased risk of hypertensive reactions when FORFIVO XL is used concomitantly with MAOIs. The use of FORFIVO XL within 14 days of discontinuing treatment with an MAOI is also contraindicated. Starting FORFIVO XL in a patient treated with reversible MAOIs such as linezolid or intravenous methylene blue is contraindicated [see Dosage and Administration (2.8), Warnings and Precautions (5.4), and Drug Interactions (7.6)].
6. FORFIVO XL is contraindicated in patients with known hypersensitivity to bupropion or the other ingredients of FORFIVO XL tablets. Anaphylactoid/anaphylactic reactions and Stevens-Johnson syndrome have been reported [see Warnings and Precautions (5.8)].

5 WARNINGS AND PRECAUTIONS

5.1 Suicidal Thoughts and Behaviors in Children, Adolescents, and Young Adults

Patients with MDD, both adult and pediatric, may experience worsening of their depression and/or the emergence of suicidal ideation and behavior (suicidality) or unusual changes in behavior, whether or not they are taking antidepressant medications, and this risk may persist until significant remission occurs. Suicide is a known risk of depression and certain other psychiatric disorders, and these disorders themselves are the strongest predictors of suicide. There has been a long-standing concern that antidepressants may have a role in inducing worsening of depression and the emergence of suicidality in certain patients during the early phases of treatment.

Pooled analyses of short-term, placebo-controlled trials of antidepressant drugs (SSRIs and others) show that these drugs increase the risk of suicidal thinking and behavior (suicidality) in children, adolescents, and young adults (ages 18 to 24) with MDD and other psychiatric disorders. Short-term studies did not show an increase in the risk of suicidality with antidepressants compared to placebo in adults beyond age 24; there was a reduction with antidepressants compared to placebo in adults aged 65 and older.

The pooled analyses of placebo-controlled trials in children and adolescents with MDD, obsessive compulsive disorder (OCD), or other psychiatric disorders included a total of 24 short-term trials of 9 antidepressant drugs in over 4,400 patients. The pooled analyses of placebo-controlled trials in adults with MDD or other psychiatric disorders included a total of 295 short-term trials (median duration of 2 months) of 11 antidepressant drugs in over 77,000 patients. There was considerable variation in risk of suicidality among drugs, but a tendency toward an increase in the younger patients for almost all drugs studied. There were differences in absolute risk of suicidality across the different indications, with the highest incidence in MDD. The risk differences (drug vs placebo), however, were relatively stable within age strata and across indications. These risk differences (drug-placebo difference in the number of cases of suicidality per 1,000 patients treated) are provided in Table 1.

Table 1. Risk Differences in the Number of Suicidality Cases by Age Group in the Pooled Placebo-controlled Trials of Antidepressants in Pediatric and Adult Patients
Age Range (Years) | Drug-Placebo Difference in Number of Cases of Suicidality per 1000 Patients Treated
 | Increases Compared to Placebo
< 18 | 14 additional cases
18-24 | 5 additional cases
 | Decreases Compared to Placebo
25-64 | 1 fewer case
≥ 65 | 6 fewer cases

No suicides occurred in any of the pediatric trials. There were suicides in the adult trials, but the number was not sufficient to reach any conclusion about drug effect on suicide.

It is unknown whether the suicidality risk extends to longer-term use, i.e., beyond several months. However, there is substantial evidence from placebo-controlled maintenance trials in adults with depression that the use of antidepressants can delay the recurrence of depression.

All patients being treated with antidepressants for any indication should be monitored appropriately and observed closely for clinical worsening, suicidality, and unusual changes in behavior, especially during the initial few months of a course of drug therapy, or at times of dose changes, either increases or decreases [see Boxed Warning and Use in Specific Populations (8.4)].

The following symptoms, anxiety, agitation, panic attacks, insomnia, irritability, hostility, aggressiveness, impulsivity, akathisia (psychomotor restlessness), hypomania, and mania have been reported in adult and pediatric patients being treated with antidepressants for MDD as well as for other indications, both psychiatric and nonpsychiatric. Although a causal link between the emergence of such symptoms and either the worsening of depression and/or the emergence of suicidal impulses has not been established, there is concern that such symptoms may represent precursors to emerging suicidality.

Consideration should be given to changing the therapeutic regimen, including possibly discontinuing the medication, in patients whose depression is persistently worse, or who are experiencing emergent suicidality or symptoms that might be precursors to worsening depression or suicidality, especially if these symptoms are severe, abrupt in onset, or were not part of the patient’s presenting symptoms.

Families and caregivers of patients being treated with antidepressants for MDD or other indications, both psychiatric and nonpsychiatric, should be alerted about the need to monitor patients for the emergence of agitation, irritability, unusual changes in behavior, and the other symptoms described above, as well as the emergence of suicidality, and to report such symptoms immediately to healthcare providers. Such monitoring should include daily observation by families and caregivers [see Patient Counseling Information (17)]. Prescriptions for FORFIVO XL should be written for the smallest quantity of tablets consistent with good patient management, in order to reduce the risk of overdose.

5.2 Neuropsychiatric Adverse Events and Suicide Risk in Smoking Cessation Treatment

FORFIVO XL is not approved for smoking cessation treatment; however, bupropion hydrochloride sustained-release is approved for this use. Serious neuropsychiatric adverse events have been reported in patients taking bupropion for smoking cessation. These postmarketing reports have included changes in mood (including depression and mania), psychosis, hallucinations, paranoia, delusions, homicidal ideation, aggression, hostility, agitation, anxiety, and panic, as well as suicidal ideation, suicide attempt, and completed suicide [see Adverse Reactions (6.2)]. Some patients who stopped smoking may have been experiencing symptoms of nicotine withdrawal, including depressed mood. Depression, rarely including suicidal ideation, has been reported in smokers undergoing a smoking cessation attempt without medication. However, some of these adverse events occurred in patients taking bupropion who continued to smoke.

Neuropsychiatric adverse events occurred in patients without and with pre-existing psychiatric disease; some patients experienced worsening of their psychiatric illnesses. Observe patients for the occurrence of neuropsychiatric adverse events. Advise patients and caregivers that the patient should stop taking FORFIVO XL and contact a healthcare provider immediately if agitation, depressed mood, or changes in behavior or thinking that are not typical for the patient are observed, or if the patient develops suicidal ideation or suicidal behavior. In many postmarketing cases, resolution of symptoms after discontinuation of bupropion was reported. The healthcare provider should evaluate the severity of the adverse events and the extent to which the patient is benefiting from treatment, and consider options including continued treatment under closer monitoring, or discontinuing treatment. In many postmarketing cases, resolution of symptoms after discontinuation of bupropion was reported. However, the symptoms persisted in some cases; therefore, ongoing monitoring and supportive care should be provided until symptoms resolve.

5.3 Seizure

Bupropion can cause seizure. The risk of seizure is dose related. Discontinue FORFIVO XL and do not restart treatment if the patient experiences a seizure.

The risk of seizures is also related to patient factors, clinical situations, and concomitant medications that lower the seizure threshold. Consider these risks before initiating treatment with FORFIVO XL. FORFIVO XL is contraindicated in patients with a seizure disorder or conditions that increase the risk of seizure (e.g., severe head injury, arteriovenous malformation, central nervous system [CNS] tumor or CNS infection, severe stroke, anorexia nervosa or bulimia, or abrupt discontinuation of alcohol, benzodiazepines, barbiturates, and antiepileptic drugs) [see Contraindications (4)]. The following conditions can also increase the risk of seizure: concomitant use of other medications that lower the seizure threshold (e.g., other bupropion products, antipsychotics, tricyclic antidepressants, theophylline, and systemic corticosteroids), metabolic disorders (e.g., hypoglycemia, hyponatremia, severe hepatic impairment, and hypoxia), or use of illicit drugs (e.g., cocaine) or abuse or misuse of prescription drugs such as CNS stimulants. Additional predisposing conditions include diabetes mellitus treated with oral hypoglycemic drugs or insulin, use of anorectic drugs, excessive use of alcohol, use of benzodiazepines, sedatives/hypnotics, or opiates.

Incidence of Seizure with Bupropion Use

The incidence of seizure with bupropion extended-release has not been formally evaluated in clinical trials. In studies using bupropion hydrochloride sustained-release up to 300 mg/day, the incidence of seizure was approximately 0.1% (1/1,000 patients). In a large prospective, follow-up study, the seizure incidence was approximately 0.4% (13/3,200 patients) with bupropion hydrochloride immediate-release in the range of 300 to 450 mg/day.

Additional data accumulated for bupropion immediate-release suggests that the estimated seizure incidence increases almost tenfold between 450 and 600 mg/day. The 600 mg dose is twice the usual adult dose and one and one-third the maximum recommended daily dose (450 mg) of FORFIVO XL. This disproportionate increase in seizure incidence with dose incrementation calls for caution in dosing.

5.4 Hypertension

Treatment with FORFIVO XL can result in elevated blood pressure and hypertension. Assess blood pressure before initiating treatment with FORFIVO XL, and monitor periodically during treatment. The risk of hypertension is increased if FORFIVO XL is used concomitantly with MAOIs or other drugs that increase dopaminergic or noradrenergic activity [see Contraindications (4)].

Data from a comparative trial of the sustained-release formulation of bupropion hydrochloride, nicotine transdermal system (NTS), the combination of sustained-release bupropion hydrochloride plus NTS, and placebo as an aid to smoking cessation suggest a higher incidence of treatment-emergent hypertension in patients treated with the combination of sustained-release bupropion hydrochloride and NTS. In this trial, 6.1% of subjects treated with the combination of sustained-release bupropion and NTS had treatment-emergent hypertension compared to 2.5%, 1.6%, and 3.1% of subjects treated with sustained-release bupropion, NTS, and placebo, respectively. The majority of these subjects had evidence of pre-existing hypertension. Three subjects (1.2%) treated with the combination of sustained-release bupropion and NTS and 1 subject (0.4%) treated with NTS had study medication discontinued due to hypertension compared with none of the subjects treated with sustained-release bupropion or placebo. Monitoring of blood pressure is recommended in patients who receive the combination of bupropion and nicotine replacement.

In a clinical trial of bupropion immediate-release in MDD subjects with stable congestive heart failure (N = 36), bupropion was associated with an exacerbation of pre-existing hypertension in 2 patients, leading to discontinuation of bupropion treatment. There are no controlled studies assessing the safety of bupropion in patients with a recent history of myocardial infarction or unstable cardiac disease.

5.5 Activation of Mania/Hypomania

Antidepressant treatment can precipitate a manic, mixed, or hypomanic manic episode. The risk appears to be increased in patients with bipolar disorder or who have risk factors for bipolar disorder. Prior to initiating FORFIVO XL, screen patients for a history of bipolar disorder and the presence of risk factors for bipolar disorder (e.g., family history of bipolar disorder, suicide, or depression). FORFIVO XL is not approved for the treatment of bipolar depression.

5.6 Psychosis and Other Neuropsychiatric Reactions

Depressed patients treated with bupropion have had a variety of neuropsychiatric signs and symptoms, including delusions, hallucinations, psychosis, concentration disturbance, paranoia, and confusion. Some of these patients had a diagnosis of bipolar disorder. In some cases, these symptoms abated upon dose reduction and/or withdrawal of treatment. Discontinue FORFIVO XL if these reactions occur.

5.7 Angle-closure Glaucoma

Angle-closure Glaucoma: The pupillary dilation that occurs following use of many antidepressant drugs including FORFIVO XL may trigger an angle closure attack in a patient with anatomically narrow angles who does not have a patent iridectomy.

5.8 Hypersensitivity Reactions

Anaphylactoid/anaphylactic reactions have occurred during clinical trials with bupropion. Reactions have been characterized by symptoms such as pruritus, urticaria, angioedema, and dyspnea, requiring medical treatment. In addition, there have been rare, spontaneous postmarketing reports of erythema multiforme, Stevens-Johnson syndrome, and anaphylactic shock associated with bupropion. Instruct patients to discontinue FORFIVO XL and consult a healthcare provider if they develop an allergic or anaphylactoid/anaphylactic reaction (e.g., skin rash, pruritus, hives, chest pain, edema, and shortness of breath) during treatment.

There are reports of arthralgia, myalgia, fever with rash, and other symptoms of serum sickness suggestive of delayed hypersensitivity.

6 ADVERSE REACTIONS

The following adverse reactions are discussed in greater detail in other sections of the labeling:

1. Suicidal thoughts and behaviors in children, adolescents, and young adults [see Warnings and Precautions (5.1)]
2. Neuropsychiatric adverse events and suicide risk in smoking cessation treatment [see Warnings and Precautions (5.2)]
3. Seizure [see Warnings and Precautions (5.3)]
4. Hypertension [see Warnings and Precautions (5.4)]
5. Activation of mania or hypomania [see Warnings and Precautions (5.5)]
6. Psychosis and other neuropsychiatric events [see Warnings and Precautions (5.6)]
7. Angle-closure Glaucoma [see Warnings and Precautions (5.7)]
8. Hypersensitivity reactions [see Warnings and Precautions (5.8)]

6.1 Clinical Trials Experience

Because clinical trials are conducted under widely varying conditions, adverse reaction rates observed in the clinical trials of a drug cannot be directly compared to rates in the clinical trials of another drug and may not reflect the rates observed in clinical practice.

Commonly Observed Adverse Reactions in Controlled Clinical Trials of Sustained-release Bupropion Hydrochloride

Adverse reactions that occurred in at least 5% of patients treated with bupropion hydrochloride sustained-release (300 and 400 mg/day) and at a rate at least twice the placebo rate are listed below.

300 mg/day of bupropion hydrochloride sustained-release: anorexia, dry mouth, rash, sweating, tinnitus, and tremor.

400 mg/day of bupropion hydrochloride sustained-release: abdominal pain, agitation, anxiety, dizziness, dry mouth, insomnia, myalgia, nausea, palpitation, pharyngitis, sweating, tinnitus, and urinary frequency.

FORFIVO XL is bioequivalent to three 150 mg tablets of WELLBUTRIN XL®, which has been demonstrated to have similar bioavailability both to the immediate-release and the sustained-release formulations of bupropion. The information included under this subsection and under subsection 6.2 is based primarily on data from controlled clinical trials with the sustained-release and extended-release formulations of bupropion hydrochloride.

Major Depressive Disorder

Adverse Reactions Leading to Discontinuation of Treatment with Bupropion Hydrochloride Immediate-release, Bupropion Hydrochloride Sustained-release, and Bupropion Hydrochloride Extended-release Formulations in Major Depressive Disorder Trials

In placebo-controlled clinical trials with bupropion hydrochloride sustained-release, 4%, 9%, and 11% of the placebo, 300 mg/day, and 400 mg/day groups, respectively, discontinued treatment because of adverse reactions. The specific adverse reactions leading to discontinuation in at least 1% of the 300 mg/day or 400 mg/day groups and at a rate at least twice the placebo rate are listed in Table 2.

Table 2. Treatment Discontinuation Due to Adverse Reactions in Placebo-controlled Trials in Major Depressive Disorder
Adverse Reaction Term | Placebo (N = 385) | Bupropion Hydrochloride Sustained-release 300 mg/day (N = 376) | Bupropion Hydrochloride Sustained-release 400 mg/day (N = 114)
Rash | 0.0% | 2.4% | 0.9%
Nausea | 0.3% | 0.8% | 1.8%
Agitation | 0.3% | 0.3% | 1.8%
Migraine | 0.3% | 0.0% | 1.8%

In clinical trials with bupropion hydrochloride immediate-release, 10% of patients and volunteers discontinued due to an adverse reaction. Reactions resulting in discontinuation (in addition to those listed above for the sustained-release formulation) included vomiting, seizures, and sleep disturbances.

Adverse Reactions Occurring at an Incidence of > 1% in Patients Treated With Bupropion Hydrochloride Immediate-release or Bupropion Hydrochloride Sustained-release Formulations in Major Depressive Disorder Trials

Table 3 summarizes the adverse reactions that occurred in placebo-controlled trials in patients treated with bupropion hydrochloride sustained-release at 300 mg/day and 400 mg/day. These include reactions that occurred in either the 300 mg/day or 400 mg/day group at an incidence of 1% or more and were more frequent than in the placebo group.

Table 3. Adverse Reactions in Placebo-controlled Trials for Major Depressive Disorder
Body System/Adverse Reaction | Placebo; (N = 385) | Bupropion Hydrochloride Sustained-release 300 mg/day (N = 376) | Bupropion Hydrochloride Sustained-release 400 mg/day (N = 114)
Body (General)
Headache | 23% | 26% | 25%
Infection | 6% | 8% | 9%
Abdominal pain | 2% | 3% | 9%
Asthenia | 2% | 2% | 4%
Chest pain | 1% | 3% | 4%
Pain | 2% | 2% | 3%
Fever | — | 1% | 2%
Cardiovascular
Palpitation | 2% | 2% | 6%
Flushing | — | 1% | 4%
Migraine | 1% | 1% | 4%
Hot flashes | 1% | 1% | 3%
Digestive
Dry mouth | 7% | 17% | 24%
Nausea | 8% | 13% | 18%
Constipation | 7% | 10% | 5%
Diarrhea | 6% | 5% | 7%
Anorexia | 2% | 5% | 3%
Vomiting | 2% | 4% | 2%
Dysphagia | 0% | 0% | 2%
Musculoskeletal
Myalgia | 3% | 2% | 6%
Arthralgia | 1% | 1% | 4%
Arthritis | 0% | 0% | 2%
Twitch | — | 1% | 2%
Nervous System
Insomnia | 6% | 11% | 16%
Dizziness | 5% | 7% | 11%
Agitation | 2% | 3% | 9%
Anxiety | 3% | 5% | 6%
Tremor | 1% | 6% | 3%
Nervousness | 3% | 5% | 3%
Somnolence | 2% | 2% | 3%
Irritability | 2% | 3% | 2%
Memory decreased | 1% | — | 3%
Paresthesia | 1% | 1% | 2%
Central nervous system stimulation | 1% | 2% | 1%
Respiratory
Pharyngitis | 2% | 3% | 11%
Sinusitis | 2% | 3% | 1%
Increased cough | 1% | 1% | 2%
Skin
Sweating | 2% | 6% | 5%
Rash | 1% | 5% | 4%
Pruritus | 2% | 2% | 4%
Urticaria | 0% | 2% | 1%
Special Senses
Tinnitus | 2% | 6% | 6%
Taste perversion | — | 2% | 4%
Blurred vision or diplopia | 2% | 3% | 2%
Urogenital
Urinary frequency | 2% | 2% | 5%
Urinary urgency | 0% | — | 2%
Vaginal hemorrhagea | — | 0% | 2%
Urinary tract infection | — | 1% | 0%
a = Incidence based on the number of female patients.
— = Denotes adverse reactions occurring in greater than 0 but less than 0.5% of patients.

The following additional adverse reactions occurred in controlled trials of bupropion hydrochloride immediate-release (300 to 600 mg/day) at an incidence of at least 1% more frequently than in the placebo group: cardiac arrhythmia (5% vs 4%), hypertension (4% vs 2%), hypotension (3% vs 2%), menstrual complaints (5% vs 1%), akathisia (2% vs 1%), impaired sleep quality (4% vs 2%), sensory disturbance (4% vs 3%), confusion (8% vs 5%), decreased libido (3% vs 2%), hostility (6% vs 4%), auditory disturbance (5% vs 3%), and gustatory disturbance (3% vs 1%).

Changes in Body Weight

Table 4 presents the incidence of body weight changes (≥ 5 lbs) in the short-term MDD trials using bupropion hydrochloride sustained-release. There was a dose-related decrease in body weight.

Table 4. Incidence of Weight Gain or Weight Loss (≥ 5 lbs) in Placebo-controlled Trials of Bupropion Hydrochloride Sustained-release Tablets for Major Depressive Disorder
Weight Change | Placebo (N = 347) | Bupropion Hydrochloride Sustained-release 300 mg/day (N = 339) | Bupropion Hydrochloride Sustained-release 400 mg/day (N = 112)
Gained > 5 lbs | 4% | 3% | 2%
Lost > 5 lbs | 6% | 14% | 19%

6.2 Postmarketing Experience

The following adverse reactions have been identified during postapproval use of bupropion hydrochloride. Because these reactions are reported voluntarily from a population of uncertain size, it is not always possible to reliably estimate their frequency or establish a causal relationship to drug exposure.

Body (General): chills, facial edema, edema, peripheral edema, musculoskeletal chest pain, photosensitivity, and malaise.

Cardiovascular: postural hypotension, hypertension, stroke, vasodilation, syncope, complete atrioventricular block, extrasystoles, myocardial infarction, phlebitis, pulmonary embolism, and Brugada pattern/syndrome.

Digestive: abnormal liver function, bruxism, gastric reflux, gingivitis, glossitis, increased salivation, jaundice, mouth ulcers, stomatitis, thirst, edema of tongue, colitis, esophagitis, gastrointestinal hemorrhage, gum hemorrhage, hepatitis, intestinal perforation, liver damage, pancreatitis, and stomach ulcer.

Endocrine: hyperglycemia, hypoglycemia, and syndrome of inappropriate antidiuretic hormone secretion.

Hemic and Lymphatic: ecchymosis, anemia, leukocytosis, leukopenia, lymphadenopathy, pancytopenia, and thrombocytopenia. Altered PT and/or INR, associated with hemorrhagic or thrombotic complications, were observed when bupropion was coadministered with warfarin.

Metabolic and Nutritional: glycosuria.

Musculoskeletal: leg cramps, fever/rhabdomyolysis, and muscle weakness.

Nervous System: abnormal coordination, depersonalization, emotional lability, hyperkinesia, hypertonia, hypesthesia, vertigo, amnesia, ataxia, derealization, abnormal electroencephalogram (EEG), aggression, akinesia, aphasia, coma, dysarthria, dyskinesia, dystonia, euphoria, extrapyramidal syndrome, hypokinesia, increased libido, neuralgia, neuropathy, paranoid ideation, restlessness, suicide attempt, and unmasking tardive dyskinesia and aseptic meningitis.

Respiratory: bronchospasm and pneumonia.

Skin and subcutaneous tissue disorders: maculopapular rash, alopecia, angioedema, exfoliative dermatitis, hirsutism, Stevens-Johnson syndrome, acute generalized exanthematous pustulosis, and drug reaction with eosinophilia and systemic symptoms (DRESS).

Special Senses: accommodation abnormality, dry eye, deafness, increased intraocular pressure, angle-closure glaucoma, and mydriasis.

Urogenital: impotence, polyuria, prostate disorder, abnormal ejaculation, cystitis, dyspareunia, dysuria, gynecomastia, menopause, painful erection, salpingitis, urinary incontinence, urinary retention, and vaginitis.

7 DRUG INTERACTIONS

7.1 Potential for Other Drugs to Affect FORFIVO XL

Bupropion is primarily metabolized to hydroxybupropion by CYP2B6. Therefore, the potential exists for drug interactions between FORFIVO XL and drugs that are inhibitors or inducers of CYP2B6.

Inhibitors of CYP2B6

Ticlopidine and Clopidogrel: Concomitant treatment with these drugs can increase bupropion exposures but decrease hydroxybupropion exposure. Coadministration of FORFIVO XL with ticlopidine or clopidogrel is not recommended [see Clinical Pharmacology (12.3)].

Inducers of CYP2B6

Ritonavir, Lopinavir, and Efavirenz: Concomitant treatment with these drugs can decrease bupropion and hydroxybupropion exposure. Patients receiving any of these drugs with bupropion may need increased doses of bupropion, but the maximum recommended dose of bupropion should not be exceeded [see Clinical Pharmacology (12.3)].

Carbamazepine, Phenobarbital, and Phenytoin: Although not systematically studied, these drugs may induce metabolism of bupropion and may decrease bupropion exposure [see Clinical Pharmacology (12.3)]. If bupropion is used concomitantly with a CYP inducer, it may be necessary to increase the dose of bupropion but the maximum recommended dose should not be exceeded.

7.2 Potential for FORFIVO XL to Affect Other Drugs

Drugs Metabolized by CYP2D6

Bupropion and its metabolites (erythrohydrobupropion, threohydrobupropion, and hydroxybupropion) are CYP2D6 inhibitors. Therefore, coadministration of bupropion with drugs that are metabolized by CYP2D6 can increase the exposures of drugs that are substrates of CYP2D6. Such drugs include antidepressants (e.g., venlafaxine, nortriptyline, imipramine, desipramine, paroxetine, fluoxetine, and sertraline), antipsychotics (e.g., haloperidol, risperidone, and thioridazine), beta-blockers (e.g., metoprolol), and Type 1C antiarrhythmics (e.g., propafenone, and flecainide). When used concomitantly with bupropion, it may be necessary to decrease the dose of these CYP2D6 substrates, particularly for drugs with a narrow therapeutic index.

Drugs that require metabolic activation by CYP2D6 to be effective (e.g., tamoxifen) theoretically could have reduced efficacy when administered concomitantly with inhibitors of CYP2D6 such as bupropion. Patients treated concomitantly with FORFIVO XL and such drugs may require increased doses of the drug [see Clinical Pharmacology (12.3)].

7.3 Drugs that Lower Seizure Threshold

Because there is no lower strength for FORFIVO XL, concurrent administration of FORFIVO XL tablets and agents that lower the seizure threshold (e.g., other bupropion products, antipsychotics, antidepressants, theophylline, or systemic corticosteroids) should be undertaken only with extreme caution [see Warnings and Precautions (5.3)].

7.4 Dopaminergic Drugs (Levodopa and Amantadine)

Bupropion, levodopa, and amantadine have dopamine agonist effects. CNS toxicity has been reported when bupropion was coadministered with levodopa or amantadine. Adverse reactions have included restlessness, agitation, tremor, ataxia, gait disturbance, vertigo, and dizziness. It is presumed that the toxicity results from cumulative dopamine agonist effects. Because there is no lower strength for FORFIVO XL, administration of FORFIVO XL tablets to patients receiving either levodopa or amantadine concurrently should be undertaken with caution.

7.5 Use with Alcohol

In postmarketing experience, there have been rare reports of adverse neuropsychiatric events or reduced alcohol tolerance in patients who were drinking alcohol during treatment with bupropion. Alcohol increased the release rate of FORFIVO XL in vitro. The consumption of alcohol during treatment with FORFIVO XL should be avoided.

7.6 Monoamine Oxidase Inhibitors (MAOIs)

Bupropion inhibits the reuptake of dopamine and norepinephrine. Concomitant use of MAOIs and bupropion is contraindicated because there is an increased risk of hypertensive reactions if bupropion is used concomitantly with MAOIs. Studies in animals demonstrate that the acute toxicity of bupropion is enhanced by the MAOI phenelzine. At least 14 days should elapse between discontinuation of an MAOI intended to treat depression and initiation of treatment with FORFIVO XL. Conversely, at least 14 days should be allowed after stopping FORFIVO XL before starting an MAOI antidepressant [see Dosage and Administration (2.7, 2.8) and Contraindications (4)].

7.7 Drug-Laboratory Test Interactions

False-positive urine immunoassay screening tests for amphetamines have been reported in patients taking bupropion. This is due to lack of specificity of some screening tests. False-positive test results may result even following discontinuation of bupropion therapy. Confirmatory tests such as gas chromatography/mass spectrometry, will distinguish bupropion from amphetamines.

8 USE IN SPECIFIC POPULATIONS

8.1 Pregnancy

Pregnancy Exposure Registry

There is a pregnancy exposure registry that monitors pregnancy outcomes in women exposed to antidepressants during pregnancy. Healthcare providers are encouraged to register patients by calling the National Pregnancy Registry for Antidepressants at 1-844-405-6185 or visiting online at https://womensmentalhealth.org/clinical-and-research-programs/pregnancyregistry/antidepressants/.

Risk Summary

Data from epidemiological studies of pregnant women exposed to bupropion in the first trimester have not identified an increased risk of congenital malformations overall (see Data). There are risks to the mother associated with untreated depression (see Clinical Considerations). When bupropion was administered to pregnant rats during organogenesis, there was no evidence of fetal malformations at doses up to approximately 10 times the maximum recommended human dose (MRHD) of 450 mg/day. When given to pregnant rabbits during organogenesis, non-dose-related increases in incidence of fetal malformations and skeletal variations were observed at doses approximately equal to the MRHD and greater. Decreased fetal weights were seen at doses twice the MRHD and greater (see Data).

The estimated background risk for major birth defects and miscarriage are unknown for the indicated population. All pregnancies have a background rate of birth defect, loss, or other adverse outcomes. In the U.S. general population, the estimated background risk of major birth defects and miscarriage in clinically recognized pregnancies is 2% to 4% and 15% to 20%, respectively.

Clinical Considerations

Disease-associated maternal and/or embryo/fetal risk

A prospective, longitudinal study followed 201 pregnant women with a history of major depressive disorder who were euthymic and taking antidepressants during pregnancy at the beginning of pregnancy. The women who discontinued antidepressants during pregnancy were more likely to experience a relapse of major depression than women who continued antidepressants. Consider the risks to the mother of untreated depression and potential effects on the fetus when discontinuing or changing treatment with antidepressant medications during pregnancy and postpartum.

Data

Human Data

Data from the international bupropion Pregnancy Registry (675 first-trimester exposures) and a retrospective cohort study using the United Healthcare database (1,213 first-trimester exposures) did not show an increased risk for malformations overall. The Registry was not designed or powered to evaluate specific defects but suggested a possible increase in cardiac malformations.

No increased risk for cardiovascular malformations overall has been observed after bupropion exposure during the first trimester. The prospectively observed rate of cardiovascular malformations in pregnancies with exposure to bupropion in the first trimester from the international Pregnancy Registry was 1.3% (9 cardiovascular malformations/675 first-trimester maternal bupropion exposures), which is similar to the background rate of cardiovascular malformations (approximately 1%). Data from the United Healthcare database, which has a limited number of exposed cases with cardiovascular malformations, and a case-controlled study (6,853 infants with cardiovascular malformations and 5,753 with non-cardiovascular malformations) from the National Birth Defects Prevention Study (NBDPS) did not show an increased risk for cardiovascular malformations overall after bupropion exposure during the first trimester.

Study findings on bupropion exposure during the first trimester and risk for left ventricular outflow tract obstruction (LVOTO) are inconsistent and do not allow conclusions regarding possible association. The United Healthcare database lacked sufficient power to evaluate this association; the NBDPS found increased risk for LVOTO (N = 10; adjusted odds ratio (OR) = 2.6; 95% CI: 1.2, 5.7) and the Slone Epidemiology case-control study did not find increased risk for LVOTO.

Study findings on bupropion exposure during the first trimester and risk for ventricular septal defect (VSD) are inconsistent and do not allow conclusions regarding a possible drug association. The Slone Epidemiology study found an increased risk for VSD following first trimester maternal bupropion exposure (N = 17; adjusted OR = 2.5; 95% CI: 1.3, 5.0) but did not find an increased risk for any other cardiovascular malformations studied (including LVOTO as above). The NBDPS and United Healthcare database study did not find an association between first trimester maternal bupropion exposure and VSD. For the findings of LVOTO and VSD, the studies were limited by the small number of exposed cases, inconsistent findings among studies, and the potential for chance findings from multiple comparisons in case-control studies.

Animal Data

In studies conducted in pregnant rats and rabbits, bupropion was administered orally during the period of organogenesis at doses of up to 450 and 150 mg/kg/day, respectively (approximately 10 and 6 times the MRHD, respectively, on a mg/m^2 basis). There was no evidence of fetal malformations in rats. When given to pregnant rabbits, during organogenesis, non-dose-related increases in incidence of fetal malformations and skeletal variations were observed at the lowest dose tested (25 mg/kg/day, approximately equal to the MRHD on a mg/m^2 basis) and greater. Decreased fetal weights were observed at doses of 50 mg/kg/day (approximately 2 times the MRHD on a mg/m^2 basis) and greater. No maternal toxicity was evident at doses of 50 mg/kg/day or less.

In a pre- and postnatal development study, bupropion administered orally to pregnant rats at doses of up to 150 mg/kg/day (approximately 3 times the MRHD on a mg/m^2 basis) from embryonic implantation through lactation had no effect on pup growth or development.

8.2 Lactation

Risk Summary

Data from published literature report the presence of bupropion and its metabolites in human milk (see Data). There are no data on the effects of bupropion or its metabolites on milk production. Limited data from postmarketing reports have not identified a clear association of adverse reactions in the breastfed infant. The developmental and health benefits of breastfeeding should be considered along with the mother’s clinical need for FORFIVO XL and any potential adverse effects on the breastfed child from FORFIVO XL or from the underlying maternal condition.

Data

In a lactation study of ten women, levels of orally dosed bupropion and its active metabolites were measured in expressed milk. The average daily infant exposure (assuming 150 mL/kg daily consumption) to bupropion and its active metabolites was 2% of the maternal weight-adjusted dose. Postmarketing reports have described seizures in breastfed infants. The relationship of bupropion exposure and these seizures is unclear.

8.4 Pediatric Use

Safety and effectiveness in the pediatric population have not been established. When considering the use of FORFIVO XL in a child or adolescent, balance the potential risks with the clinical need [see Boxed Warning, and Warnings and Precautions (5.1)].

8.5 Geriatric Use

Of the approximately 6000 patients who participated in clinical trials with bupropion hydrochloride sustained-release tablets (depression and smoking cessation studies), 275 were ≥ 65 years of age and 47 were ≥ 75 years of age. In addition, several hundred patients ≥ 65 years of age participated in clinical trials using the immediate-release formulation of bupropion hydrochloride (depression studies). No overall differences in safety or effectiveness were observed between these subjects and younger subjects. Reported clinical experience has not identified differences in responses between the elderly and younger patients, but greater sensitivity of some older individuals cannot be ruled out.

Bupropion is extensively metabolized in the liver to active metabolites, which are further metabolized and excreted by the kidneys. The risk of adverse reactions may be greater in patients with impaired renal function. Because elderly patients are more likely to have decreased renal function, it may be necessary to consider this factor in dose selection; it may be useful to monitor renal function [see Dosage and Administration (2.6), Use in Specific Populations (8.6), and Clinical Pharmacology (12.3)].

8.6 Renal Impairment

Because there is no lower strength for FORFIVO XL, FORFIVO XL is not recommended in patients with renal impairment [see Clinical Pharmacology (12.3)].

8.7 Hepatic Impairment

Because there is no lower strength for FORFIVO XL, FORFIVO XL is not recommended in patients with hepatic impairment [see Clinical Pharmacology (12.3)].

9 DRUG ABUSE AND DEPENDENCE

9.1 Controlled Substance

Bupropion is not a controlled substance.

9.2 Abuse

Humans

Controlled clinical studies of bupropion hydrochloride (immediate-release formulation) conducted in normal volunteers, in subjects with a history of multiple drug abuse, and in depressed patients demonstrated an increase in motor activity and agitation/excitement.

In a population of individuals experienced with drugs of abuse, a single dose of 400 mg of bupropion hydrochloride produced mild amphetamine-like activity as compared to placebo on the Morphine-Benzedrine Subscale of the Addiction Research Center Inventories (ARCI), and a score intermediate between placebo and amphetamine on the Liking Scale of the ARCI. These scales measure general feelings of euphoria and drug desirability.

Findings in clinical trials, however, are not known to reliably predict the abuse potential of drugs. Nonetheless, evidence from single-dose studies does suggest that the recommended daily dosage of bupropion when administered in divided doses is not likely to be significantly reinforcing to amphetamine or CNS-stimulant abusers. However, higher doses (that could not be tested because of the risk of seizure) might be modestly attractive to those who abuse CNS-stimulant drugs.

Bupropion hydrochloride extended-release tablets are intended for oral use only. The inhalation of crushed tablets or injection of dissolved bupropion has been reported. Seizures and/or cases of death have been reported when bupropion has been administered intranasally or by parenteral injection.

Animals

Studies in rodents and primates demonstrated that bupropion exhibits some pharmacologic actions common to psychostimulants. In rodents, it has been shown to increase locomotor activity, elicit a mild stereotyped behavioral response, and increase rates of responding in several schedule-controlled behavior paradigms. In primate models assessing the positive reinforcing effects of psychoactive drugs, bupropion was self-administered intravenously. In rats, bupropion produced amphetamine-like and cocaine-like discriminative stimulus effects in drug discrimination paradigms used to characterize the subjective effects of psychoactive drugs.

10 OVERDOSAGE

10.1 Human Overdose Experience

Overdoses of up to 30 g or more of bupropion have been reported. Seizure was reported in approximately one third of all cases. Other serious reactions reported with overdoses of bupropion alone included hallucinations, loss of consciousness, mental status changes, sinus tachycardia, ECG changes such as conduction disturbances or arrhythmias, clonus, myoclonus, and hyperreflexia. Fever, muscle rigidity, rhabdomyolysis, hypotension, stupor, coma, and respiratory failure have been reported mainly when bupropion was part of multiple drug overdoses.

Although most patients recovered without sequelae, deaths associated with overdoses of bupropion alone have been reported in patients ingesting large doses of the drug. Multiple uncontrolled seizures, bradycardia, cardiac failure, and cardiac arrest prior to death were reported in these patients.

10.2 Overdosage Management

Consult a Certified Poison Control Center for up-to-date guidance and advice. Call 1-800-222-1222 or refer to www.poison.org.

There are no known antidotes for bupropion. In case of an overdose, provide supportive care, including close medical supervision and monitoring. Consider the possibility of multiple drug overdose.

11 DESCRIPTION

FORFIVO XL (bupropion hydrochloride), an antidepressant of the aminoketone class, is chemically unrelated to tricyclic, tetracyclic, selective serotonin re-uptake inhibitor, or other known antidepressant agents. Its structure closely resembles that of diethylpropion; it is related to phenylethylamines. It is designated as (±)-2-(tert-Butylamino)-3'-chloropropiophenone hydrochloride. The molecular weight is 276.2. The empirical formula is C13H18ClNO·HCl. Bupropion hydrochloride powder is white or almost white, crystalline, and soluble in water. It has a bitter taste and produces the sensation of local anesthesia on the oral mucosa. The structural formula is:

FORFIVO XL tablets are supplied for oral administration of 450 mg of bupropion hydrochloride as white to off-white extended-release tablets. Each film-coated tablet contains the labeled amount of bupropion hydrochloride and the inactive ingredients: carboxymethyl cellulose sodium, colloidal silicon dioxide, hydrochloric acid, hydroxypropyl cellulose, hypromellose, magnesium stearate, methacrylic acid copolymer, polyethylene glycol 8000, polyethylene oxide, polyvinyl pyrrolidone and polyvinyl acetate blend, stearic acid, talc, titanium dioxide and triacetin. The logo “Forfivo” is printed on one side of the tablet with edible black ink.

12 CLINICAL PHARMACOLOGY

12.1 Mechanism of Action

The mechanism of action of bupropion is unknown, as is the case with other antidepressants. However, it is presumed that this action is mediated by noradrenergic and/or dopaminergic mechanisms. Bupropion is a relatively weak inhibitor of the neuronal uptake of norepinephrine and dopamine, and does not inhibit monoamine oxidase or the reuptake of serotonin.

12.3 Pharmacokinetics

Bupropion is a racemic mixture. The pharmacologic activity and pharmacokinetics of the individual enantiomers have not been studied.

Following single dosing under fasted conditions of FORFIVO XL tablets, the maximum peak plasma concentration (Cmax), and the area under the plasma concentration versus time curve of bupropion from zero to infinity (AUCinf), were 207.46 (± 59.40) ng/mL, and 2147.53 (± 664.12) ng•hr/mL, respectively. The elimination half-life (± SD) of bupropion after a single dose was 14.44 (± 5.00) hours.

In a single-dose study under fasting conditions, one FORFIVO XL tablet given once daily and three WELLBUTRIN XL 150 mg tablets once daily were evaluated. Equivalence was demonstrated for peak concentration and area under the curve for bupropion and the 3 metabolites (hydroxybupropion, erythrohydrobupropion, and threohydrobupropion).

Absorption

Following single oral administration of FORFIVO XL tablets to healthy volunteers, the median time to peak plasma concentrations for bupropion was approximately 5 hours under fasted conditions, and 12 hours under fed conditions. The presence of food did not affect the maximum peak plasma concentration for bupropion, however, mean systemic exposure to bupropion was increased by 25% when FORFIVO XL tablets were taken with food. The food effect is not considered clinically significant and FORFIVO XL can be taken with or without food.

Distribution

In vitro tests show that bupropion is 84% bound to human plasma proteins at concentrations up to 200 mcg/mL. The extent of protein binding of the hydroxybupropion metabolite is similar to that for bupropion, whereas the extent of protein binding of the threohydrobupropion metabolite is about half that of bupropion.

Metabolism

Bupropion is extensively metabolized in humans. Three metabolites are active: hydroxybupropion, which is formed via hydroxylation of the tert-butyl group of bupropion, and the amino-alcohol isomers threohydrobupropion and erythrohydrobupropion, which are formed via reduction of the carbonyl group. In vitro findings suggest that CYP2B6 is the principal isoenzyme involved in the formation of hydroxybupropion, while cytochrome P450 isoenzymes are not involved in the formation of threohydrobupropion. Oxidation of the bupropion side chain results in the formation of a glycine conjugate of meta-chlorobenzoic acid, which is then excreted as the major urinary metabolite. The potency and toxicity of the metabolites relative to bupropion have not been fully characterized. However, it has been demonstrated in an antidepressant screening test in mice that hydroxybupropion is one half as potent as bupropion, while threohydrobupropion and erythrohydrobupropion are 5-fold less potent than bupropion. This may be of clinical importance because the plasma concentrations of the metabolites are as high or higher than those of bupropion.

In humans, peak plasma concentrations of hydroxybupropion occur approximately 10 hours after administration of a single dose of FORFIVO XL under fasted conditions and 16 hours under fed conditions. Following administration of WELLBUTRIN XL, peak plasma concentrations of hydroxybupropion are approximately 7 times the peak level of the parent drug at steady state. The elimination half-life of hydroxybupropion is approximately 20 (± 5) hours, and its AUC at steady state is about 13 times that of bupropion. The times to peak concentrations for the erythrohydrobupropion and threohydrobupropion metabolites are similar to that of the hydroxybupropion metabolite. However, the elimination half-lives of erythrohydrobupropion and threohydrobupropion are longer, approximately 33 (± 10) and 37 (± 13) hours, respectively, and steady-state AUCs are 1.4 and 7 times that of bupropion, respectively.

Bupropion and its metabolites exhibit linear kinetics following chronic administration of 300 to 450 mg/day of bupropion hydrochloride.

Elimination

Following oral administration of 200 mg of ^14C-bupropion in humans, 87% and 10% of the radioactive dose were recovered in the urine and feces, respectively. Only 0.5% of the oral dose was excreted as unchanged bupropion.

Population Subgroups

Factors or conditions altering metabolic capacity (e.g., liver disease, congestive heart failure [CHF], age, concomitant medications, etc.) or elimination may be expected to influence the degree and extent of accumulation of the active metabolites of bupropion. The elimination of the major metabolites of bupropion may be affected by reduced renal or hepatic function because they are moderately polar compounds and are likely to undergo further metabolism or conjugation in the liver prior to urinary excretion.

Renal Impairment

There is limited information on the pharmacokinetics of bupropion in patients with renal impairment. An intertrial comparison between normal subjects and patients with end-stage renal failure demonstrated that the parent drug Cmax and AUC values were comparable in the 2 groups, whereas the hydroxybupropion and threohydrobupropion metabolites had a 2.3- and 2.8-fold increase, respectively, in AUC for subjects with end-stage renal failure. A second study, comparing normal subjects and subjects with moderate to severe renal impairment (GFR 30.9 ± 10.8 mL/min) showed that after a single 150 mg dose of sustained-release bupropion, exposure to bupropion was approximately 2-fold higher in subjects with impaired renal function while levels of the hydroxybupropion and threo/erythrohydrobupropion (combined) metabolites were similar in the 2 groups. Bupropion is extensively metabolized in the liver to active metabolites, which are further metabolized and subsequently excreted by the kidneys. The elimination of the major metabolites of bupropion may be reduced by impaired renal function [see Dosage and Administration (2.6) and Use in Specific Populations (8.6)].

Hepatic Impairment

The effect of hepatic impairment on the pharmacokinetics of bupropion was characterized in 2 single-dose studies, one in subjects with alcoholic liver disease and one in subjects with mild to severe cirrhosis. The first trial demonstrated that the half-life of hydroxybupropion was significantly longer in 8 subjects with alcoholic liver disease than in 8 healthy volunteers (32 ± 14 hours versus 21 ± 5 hours, respectively). Although not statistically significant, the AUCs for bupropion and hydroxybupropion were more variable and tended to be greater (by 53% to 57%) in patients with alcoholic liver disease. The differences in half-life for bupropion and the other metabolites in the 2 groups were minimal.

The second trial demonstrated no statistically significant differences in the pharmacokinetics of bupropion and its active metabolites in 9 subjects with mild to moderate hepatic cirrhosis compared to 8 healthy volunteers. However, more variability was observed in some of the pharmacokinetic parameters for bupropion (AUC, Cmax, and Tmax) and its active metabolites (t½) in subjects with mild to moderate hepatic cirrhosis. In addition, in patients with severe hepatic cirrhosis, the bupropion Cmax and AUC were substantially increased (mean difference: by approximately 70% and 3-fold, respectively) and more variable when compared to values in healthy volunteers; the mean bupropion half-life was also longer (29 hours in subjects with severe hepatic cirrhosis vs 19 hours in healthy subjects). For the metabolite hydroxybupropion, the mean Cmax was approximately 69% lower. For the combined amino-alcohol isomers threohydrobupropion and erythrohydrobupropion, the mean Cmax was approximately 31% lower. The mean AUC increased by about 1.5-fold for hydroxybupropion and about 2.5-fold for threo/erythrohydrobupropion. The median Tmax was observed 19 hours later for hydroxybupropion and 31 hours later for threo/erythrohydrobupropion. The mean half-lives for hydroxybupropion and threo/erythrohydrobupropion were increased 5- and 2-fold, respectively, in patients with severe hepatic cirrhosis compared to healthy volunteers [see Dosage and Administration (2.5) and Use in Specific Populations (8.7)].

Left Ventricular Dysfunction

During a chronic dosing study with bupropion in 14 depressed patients with left ventricular dysfunction (history of CHF or an enlarged heart on x-ray), there was no apparent effect on the pharmacokinetics of bupropion or its metabolites, compared to healthy volunteers.

Age

The effects of age on the pharmacokinetics of bupropion and its metabolites have not been fully characterized, but an exploration of steady-state bupropion concentrations from several depression efficacy studies involving patients dosed in a range of 300 to 750 mg/day, on a 3 times daily schedule, revealed no relationship between age (18 to 83 years) and plasma concentration of bupropion. A single-dose pharmacokinetic study demonstrated that the disposition of bupropion and its metabolites in elderly subjects was similar to that in younger subjects. These data suggest that there is no prominent effect of age on bupropion concentration; however, another single- and multiple-dose pharmacokinetic study suggested that the elderly are at increased risk for accumulation of bupropion and its metabolites [see Use in Specific Populations (8.5)].

Gender

A single-dose study involving 12 healthy male and 12 healthy female volunteers revealed no sex-related differences in the pharmacokinetic parameters of bupropion. In addition, pooled analysis of bupropion pharmacokinetic data from 90 healthy male and 90 healthy female volunteers revealed no sex-related differences in the peak plasma concentrations of bupropion. The mean systemic exposure (AUC) was approximately 13% higher in male volunteers compared to female volunteers.

Smokers

The effects of cigarette smoking on the pharmacokinetics of bupropion hydrochloride were studied in 34 healthy male and female volunteers; 17 were chronic cigarette smokers and 17 were nonsmokers. Following oral administration of a single 150 mg dose of bupropion, there was no statistically significant difference in Cmax, half-life, Tmax, AUC, or clearance of bupropion or its active metabolites between smokers and nonsmokers.

Drug Interactions

Potential for Other Drugs to Affect FORFIVO XL

In vitro studies indicate that bupropion is primarily metabolized to hydroxybupropion by CYP2B6. Therefore, the potential exists for drug interactions between FORFIVO XL and drugs that are inhibitors or inducers of CYP2B6. In addition, in vitro studies suggest that paroxetine, sertraline, norfluoxetine, fluvoxamine, and nelfinavir, inhibit the hydroxylation of bupropion.

Inhibitors of CYP2B6

Ticlopidine, Clopidogrel: In a study in healthy male volunteers, clopidogrel 75 mg once daily or ticlopidine 250 mg twice daily increased exposures (Cmax and AUC) of bupropion by 40% and 60% for clopidogrel and by 38% and 85% for ticlopidine, respectively. The exposures of hydroxybupropion were decreased.

Prasugrel: In healthy subjects, prasugrel increased bupropion Cmax and AUC values by 14% and 18%, respectively, and decreased Cmax and AUC values of hydroxybupropion by 32% and 24%, respectively.

Cimetidine: Following oral administration of bupropion 300 mg with and without cimetidine 800 mg in 24 healthy young male volunteers, the pharmacokinetics of bupropion and hydroxybupropion were unaffected. However, there were 16% and 32% increases in the AUC and Cmax, respectively, of the combined moieties of threohydrobupropion and erythrohydrobupropion.

Citalopram: Citalopram did not affect the pharmacokinetics of bupropion and its 3 metabolites.

Inducers of CYP2B6

Ritonavir and Lopinavir: In a healthy volunteer study, ritonavir 100 mg twice daily reduced the AUC and Cmax of bupropion by 22% and 21%, respectively. The exposure of the hydroxybupropion metabolite was decreased by 23%, threohydrobupropion decreased by 38%, and erythrohydrobupropion decreased by 48%. In a second healthy volunteer study, ritonavir 600 mg twice daily decreased the AUC and the Cmax of bupropion by 66% and 62%, respectively. The exposure of the hydroxybupropion metabolite was decreased by 78%, threohydrobupropion decreased by 50%, and erythrohydrobupropion decreased by 68%.

In another healthy volunteer study, lopinavir 400 mg/ritonavir 100 mg twice daily decreased bupropion AUC and Cmax by 57%. The AUC and Cmax of the hydroxybupropion metabolite were decreased by 50% and 31%, respectively.

Efavirenz: In a study of healthy volunteers, efavirenz 600 mg once daily for 2 weeks reduced the AUC and Cmax of bupropion by approximately 55% and 34%, respectively. The AUC of hydroxybupropion was unchanged, whereas Cmax of hydroxybupropion was increased by 50%.

Carbamazepine, Phenobarbital, Phenytoin: Although not systematically studied, these drugs may induce the metabolism of bupropion.

Potential for FORFIVO XL to Affect Other Drugs

Animal data indicated that bupropion may be an inducer of drug-metabolizing enzymes in humans. In a study of 8 healthy male volunteers, following a 14-day administration of bupropion 100 mg 3 times daily, there was no evidence of induction of its own metabolism. Nevertheless, there may be the potential for clinically important alterations of blood levels of coadministered drugs.

Drugs Metabolized by CYP2D6

In vitro, bupropion and hydroxybupropion are CYP2D6 inhibitors. In a clinical study of 15 male subjects (19 to 35 years of age) who were extensive metabolizers of CYP2D6, bupropion given as 150 mg twice daily followed by a single dose of 50 mg desipramine increased the Cmax, AUC, and t½ of desipramine by an average of approximately 2-, 5-, and 2-fold, respectively. The effect was present for at least 7 days after the last dose of bupropion. Concomitant use of bupropion with other drugs metabolized by CYP2D6 has not been formally studied.

Citalopram: Although citalopram is not primarily metabolized by CYP2D6, in one study bupropion increased the Cmax and AUC of citalopram by 30% and 40%, respectively.

Lamotrigine: Multiple oral doses of bupropion had no statistically significant effects on the single-dose pharmacokinetics of lamotrigine in 12 healthy volunteers.

13 NONCLINICAL TOXICOLOGY

13.1 Carcinogenesis, Mutagenesis, Impairment of Fertility

Lifetime carcinogenicity studies were performed in rats and mice at doses up to 300 and 150 mg/kg/day bupropion hydrochloride, respectively. These doses are approximately 7 and 2 times the MRHD, respectively, on a mg/m^2 basis. In the rat study there was an increase in nodular proliferative lesions of the liver at doses of 100 to 300 mg/kg/day of bupropion hydrochloride (approximately 2 to 7 times the MRHD on a mg/m^2 basis); lower doses were not tested. The question of whether or not such lesions may be precursors of neoplasms of the liver is currently unresolved. Similar liver lesions were not seen in the mouse study, and no increase in malignant tumors of the liver and other organs was seen in either study.

Bupropion produced a positive response (2 to 3 times control mutation rate) in 2 of 5 strains in one Ames bacterial mutagenicity assay, but was negative in another. Bupropion produced an increase in chromosomal aberrations in 1 of 3 in vivo rat bone marrow cytogenetic studies.

A fertility study in rats at doses up to 300 mg/kg/day revealed no evidence of impaired fertility.

14 CLINICAL STUDIES

The efficacy of bupropion in the treatment of MDD was established with the immediate-release formulation of bupropion hydrochloride in two 4-week, placebo-controlled trials in adult inpatients with MDD and in one 6-week, placebo-controlled trial in adult outpatients with MDD. In the first study, the bupropion dose range was 300 to 600 mg/day administered in 3 divided doses; 78% of patients were treated with doses of 300 to 450 mg/day. The trial demonstrated the efficacy of bupropion as measured by the Hamilton Depression Rating Scale (HDRS) total score, the HDRS depressed mood item (item 1), and the Clinical Global Impressions-Severity Scale (CGI-S). The second study included 2 fixed doses of bupropion (300 and 450 mg per day) and placebo. This trial demonstrated the efficacy of bupropion for only the 450 mg dose. The efficacy results were significant for the HDRS total score and the CGI-S score, but not for HDRS item 1. In the third study, outpatients were treated with bupropion at 300 mg/day. This study demonstrated the efficacy of bupropion as measured by the HDRS total score, the HDRS item 1, the Montgomery-Asberg Depression Rating Scale (MADRS), the CGI-S score, and the CGI-Improvement Scale (CGI-I) score.

A longer-term, placebo-controlled, randomized withdrawal trial demonstrated the efficacy of bupropion hydrochloride sustained-release in the maintenance treatment of MDD. The trial included adult outpatients meeting DSM-IV criteria for MDD, recurrent type, who had responded during an 8-week open-label trial of bupropion 300 mg/day. Responders were randomized to continuation of bupropion at 300 mg/day or placebo, for up to 44 weeks of observation for relapse. Response during the open-label phase was defined as a CGI-I score of 1 (very much improved) or 2 (much improved) for each of the final 3 weeks. Relapse during the double-blind phase was defined as the investigator’s judgment that drug treatment was needed for worsening depressive symptoms. Patients in the bupropion group experienced significantly lower relapse rates over the subsequent 44 weeks compared to those in the placebo group.

Although there are no independent trials demonstrating the efficacy of bupropion extended-release in the acute treatment of MDD, studies have demonstrated similar bioavailability between the immediate-, sustained-, and extended-release formulations of bupropion hydrochloride under steady-state conditions (i.e., the exposures [Cmax and AUC] for bupropion and its metabolites are similar among the 3 formulations). Further, it has been demonstrated that FORFIVO XL is bioequivalent to WELLBUTRIN XL.

16 HOW SUPPLIED/STORAGE AND HANDLING

FORFIVO XL Extended-Release Tablets, 450 mg of bupropion hydrochloride, are white to off-white, oblong-shaped tablets printed with the “Forfivo” logo on one side supplied in bottles of 30 tablets
(NDC 24979-247-06).

Store at 20°C to 25°C (68°F to 77°F) [see USP Controlled Room Temperature].

17 PATIENT COUNSELING INFORMATION

Advise the patient to read the FDA-approved patient labeling (Medication Guide).

Suicidal Thoughts and Behaviors

Instruct patients, their families, and/or their caregivers to be alert to the emergence of anxiety, agitation, panic attacks, insomnia, irritability, hostility, aggressiveness, impulsivity, akathisia (psychomotor restlessness), hypomania, mania, other unusual changes in behavior, worsening of depression, and suicidal ideation, especially early during antidepressant treatment and when the dose is adjusted up or down. Advise families and caregivers of patients to observe for the emergence of such symptoms on a day-to-day basis, since changes may be abrupt. Such symptoms should be reported to the patient’s prescriber or health professional, especially if they are severe, abrupt in onset, or were not part of the patient’s presenting symptoms. Symptoms such as these may be associated with an increased risk for suicidal thinking and behavior and indicate a need for very close monitoring and possibly changes in the medication.

Neuropsychiatric Adverse Events and Suicide Risk in Smoking Cessation Treatment

Although FORFIVO XL is not indicated for smoking cessation treatment, it contains the same active ingredient as ZYBAN® which is approved for this use. Inform patients that some patients have experienced changes in mood (including depression and mania), psychosis, hallucinations, paranoia, delusions, homicidal ideation, aggression, hostility, agitation, anxiety, and panic, as well as suicidal ideation and suicide when attempting to quit smoking while taking bupropion. Instruct patients to discontinue FORFIVO XL and contact a healthcare professional if they experience such symptoms [see Warnings and Precautions (5.2) and Adverse Reactions (6.2)].

Severe Allergic Reactions

Educate patients on the symptoms of hypersensitivity and to discontinue FORFIVO XL if they have a severe allergic reaction.

Seizure

Instruct patients to discontinue and not restart FORFIVO XL if they experience a seizure while on treatment. Advise patients that the excessive use or the abrupt discontinuation of alcohol, benzodiazepines, antiepileptic drugs, or sedatives/hypnotics can increase the risk of seizure. Advise patients to avoid the use of alcohol.

Angle-closure Glaucoma

Patients should be advised that taking FORFIVO XL can cause mild pupillary dilation, which in susceptible individuals, can lead to an episode of angle-closure glaucoma. Pre-existing glaucoma is almost always open-angle glaucoma because angle-closure glaucoma, when diagnosed, can be treated definitively with iridectomy. Open-angle glaucoma is not a risk factor for angle-closure glaucoma. Patients may wish to be examined to determine whether they are susceptible to angle closure, and have a prophylactic procedure (e.g., iridectomy), if they are susceptible [see Warnings and Precautions (5.7)].

Bupropion-containing Products

Educate patients that FORFIVO XL contains the same active ingredient (bupropion) found in ZYBAN, which is used as an aid to smoking cessation treatment, and that FORFIVO XL should not be used in combination with ZYBAN or any other medications that contain bupropion hydrochloride (such as WELLBUTRIN XL, the extended-release formulation; WELLBUTRIN SR®, the sustained-release formulation; WELLBUTRIN®, the immediate-release formulation; and APLENZIN®, a bupropion hydrobromide formulation). In addition, there are a number of generic bupropion hydrochloride products for the immediate-, sustained-, and extended-release formulations.

Potential for Cognitive and Motor Impairment

Advise patients that any CNS-active drug like FORFIVO XL tablets may impair their ability to perform tasks requiring judgment or motor and cognitive skills. Advise patients that until they are reasonably certain that FORFIVO XL tablets do not adversely affect their performance, they should refrain from driving an automobile or operating complex, hazardous machinery. FORFIVO XL treatment may lead to decreased alcohol tolerance.

Concomitant Medications

Counsel patients to notify their healthcare provider if they are taking or plan to take any prescription or over-the-counter drugs, because FORFIVO XL tablets and other drugs may affect each other’s metabolism.

Pregnancy

Advise patients to notify their healthcare provider if they become pregnant or intend to become pregnant during therapy with FORFIVO XL. Advise patients that there is a pregnancy exposure registry that monitors pregnancy outcomes in women exposed to FORFIVO XL during pregnancy [see Use in Specific Populations (8.1)].

Administration Information

Instruct patients to swallow FORFIVO XL tablets whole so that the release rate is not altered. Instruct patients that FORFIVO XL tablets should not be chewed, divided, or crushed. FORFIVO XL may be taken with or without food.

FORFIVO XL is a registered trademark of TWi Pharmaceuticals, Inc. All other products/brand names are trademarks of their respective owners.

Manufactured by:
Pillar5 Pharma Inc.
Arnprior, Ontario K7S 0C9, Canada

Distributed by:
TWi Pharmaceuticals USA, Inc.
Paramus, NJ 07652

RL-IN000181 Revised: 11/2025

MEDICATION GUIDE

FORFIVO XL (Fore-fyel-voe Eks el)
(bupropion hydrochloride) Extended-Release Tablets

IMPORTANT: Be sure to read the three sections of this Medication Guide. The first section is about the risk of suicidal thoughts and actions with antidepressant medicines; the second section is about the risk of changes in thinking and behavior, depression and suicidal thoughts or actions with medicines used to quit smoking; and the third section is entitled “What Other Important Information Should I Know About FORFIVO XL?”

Antidepressant Medicines, Depression and Other Serious Mental Illnesses, and Suicidal Thoughts or Actions
This section of the Medication Guide is only about the risk of suicidal thoughts and actions with antidepressant medicines.
What is the most important information I should know about antidepressant medicines, depression and other serious mental illnesses, and suicidal thoughts or actions?
1. Antidepressant medicines may increase the risk of suicidal thoughts or actions in some children, teenagers, or young adults within the first few months of treatment.
2. Depression or other serious mental illnesses are the most important causes of suicidal thoughts and actions. Some people may have a particularly high risk of having suicidal thoughts or actions. These include people who have (or have a family history of) bipolar illness (also called manic-depressive illness) or suicidal thoughts or actions.
3. How can I watch for and try to prevent suicidal thoughts and actions in myself or a family member?

- Pay close attention to any changes, especially sudden changes, in mood, behaviors, thoughts, or feelings. This is very important when an antidepressant medicine is started or when the dose is changed.
- Call your healthcare provider right away to report new or sudden changes in mood, behavior, thoughts, or feelings.
- Keep all follow-up visits with your healthcare provider as scheduled. Call the healthcare provider between visits as needed, especially if you have concerns about symptoms.

Call your healthcare provider right away if you or your family member has any of the following symptoms, especially if they are new, worse, or worry you:

- thoughts about suicide or dying
- attempts to commit suicide
- new or worse depression
- new or worse anxiety
- feeling very agitated or restless
- panic attacks
- trouble sleeping (insomnia)
- new or worse irritability
- acting aggressive, being angry, or violent
- acting on dangerous impulses
- an extreme increase in activity and talking (mania)
- other unusual changes in behavior or mood

What else do I need to know about antidepressant medicines?

- Never stop an antidepressant medicine without first talking to a healthcare provider. Stopping an antidepressant medicine suddenly can cause other symptoms.
- Antidepressants are medicines used to treat depression and other illnesses. It is important to discuss all the risks of treating depression and also the risks of not treating it. Patients and their families or other caregivers should discuss all treatment choices with the healthcare provider, not just the use of antidepressants.
- Antidepressant medicines have other side effects. Talk to the healthcare provider about the side effects of the medicine prescribed for you or your family member.
- Antidepressant medicines can interact with other medicines. Know all of the medicines that you or your family member takes. Keep a list of all medicines to show the healthcare provider. Do not start new medicines without first checking with your healthcare provider.

It is not known if FORFIVO XL is safe and effective in children under the age of 18.

Quitting Smoking, Quit-Smoking Medications, Changes in Thinking and Behavior, Depression, and Suicidal Thoughts or Actions
This section of the Medication Guide is only about the risk of changes in thinking and behavior, depression and suicidal thoughts or actions with drugs used to quit smoking. Although FORFIVO XL is not a treatment for quitting smoking, it contains the same active ingredient (bupropion) as ZYBAN® which is used to help patients quit smoking.
Talk to your healthcare provider or your family member’s healthcare provider about:

- all risks and benefits of quit-smoking medicines.
- all treatment choices for quitting smoking.

When you try to quit smoking, with or without bupropion you may have symptoms that may be due to nicotine withdrawal, including:

- urge to smoke
- depressed mood
- trouble sleeping
- irritability
- frustration
- anger
- feeling anxious
- difficulty concentrating
- restlessness
- decreased heart rate
- increased appetite
- weight gain

Some people have even experienced suicidal thoughts when trying to quit smoking without medication. Sometimes quitting smoking can lead to worsening of mental health problems that you already have, such as depression.
Some people have had serious side effects while taking bupropion to help them quit smoking, including:
New or worse mental health problems, such as changes in behavior or thinking, aggression, hostility, agitation, depression, or suicidal thoughts or actions. Some people had these symptoms when they began taking bupropion, and others developed them after several weeks of treatment, or after stopping bupropion. These symptoms happened more often in people who had a history of mental health problems before taking bupropion than in people without a history of mental health problems.
Stop taking FORFIVO XL and call your healthcare provider right away if you, your family, or caregiver notice any of these symptoms. Work with your healthcare provider to decide whether you should continue to take FORFIVO XL. In many people, these symptoms went away after stopping bupropion, but in some people symptoms continued after stopping bupropion. It is important for you to follow-up with your healthcare provider until your symptoms go away. Before taking FORFIVO XL, tell your healthcare provider if you have ever had depression or other mental health problems. You should also tell your healthcare provider about any symptoms you had during other times you tried to quit smoking, with or without bupropion.

What Other Important Information Should I Know About FORFIVO XL?

- Seizures: There is a chance of having a seizure (convulsion, fit) with FORFIVO XL, especially in people:
  - with certain medical problems.
  - who take certain medicines.
  The chance of having seizures increases with higher doses of FORFIVO XL. For more information, see the sections “Who should not take FORFIVO XL?” and “What should I tell my healthcare provider before taking FORFIVO XL?” Tell your healthcare provider about all of your medical conditions and all the medicines you take. Do not take any other medicines while you are taking FORFIVO XL unless your healthcare provider has said it is okay to take them. If you have a seizure while taking FORFIVO XL, stop taking the tablets and call your healthcare provider right away. Do not take FORFIVO XL again if you have a seizure.
- High blood pressure (hypertension). Some people get high blood pressure that can be severe, while taking FORFIVO XL. The chance of high blood pressure may be higher if you also use nicotine replacement therapy (such as a nicotine patch) to help you stop smoking (see the section of this Medication Guide called “How should I take FORFIVO XL?”).
- Manic episodes.Some people may have periods of mania while taking FORFIVO XL, including:
  - Greatly increased energy
  - Severe trouble sleeping
  - Racing thoughts
  - Reckless behavior
  - Unusually grand ideas
  - Excessive happiness or irritability
  - Talking more or faster than usual
  If you have any of the above symptoms of mania, call your healthcare provider.
- Unusual thoughts or behaviors. Some patients have unusual thoughts or behaviors while taking FORFIVO XL, including delusions (believe you are someone else), hallucinations (seeing or hearing things that are not there), paranoia (feeling that people are against you), or feeling confused. If this happens to you, call your healthcare provider.
- Visual problems.
  - eye pain
  - changes in vision
  - swelling or redness in or around the eye
  Only some people are at risk for these problems. You may want to undergo an eye examination to see if you are at risk and receive preventative treatment if you are.
- Severe allergic reactions. Some people can have severe allergic reactions to FORFIVO XL. Stop taking FORFIVO XL and call your healthcare provider right away if you get a rash, itching, hives, fever, swollen lymph glands, painful sores in the mouth or around the eyes, swelling of the lips or tongue, chest pain, or have trouble breathing. These could be signs of a serious allergic reaction.

What is FORFIVO XL?
FORFIVO XL is a prescription medicine used to treat adults with a certain type of depression called major depressive disorder.

Who should not take FORFIVO XL?
Do not take FORFIVO XL if you:

- have or had a seizure disorder or epilepsy.
- have or had an eating disorder such as anorexia nervosa or bulimia.
- are taking any other medicines that contain bupropion, including WELLBUTRIN, WELLBUTRIN SR®, WELLBUTRIN XL®, ZYBAN, or APLENZIN®. Bupropion is the same active ingredient that is in FORFIVO XL.
- drink a lot of alcohol and abruptly stop drinking, or take medicines called sedatives (these make you sleepy), benzodiazepines, or anti-seizure medicines, and you stop taking them all of a sudden.
- take a monoamine oxidase inhibitor (MAOI). Ask your healthcare provider or pharmacist if you are not sure if you take an MAOI, including the antibiotic linezolid.
  - do not take an MAOI within 2 weeks of stopping FORFIVO XL unless directed to do so by your healthcare provider.
  - do not start FORFIVO XL if you stopped taking an MAOI in the last 2 weeks unless directed to do so by your healthcare provider.
- are allergic to the active ingredient in FORFIVO XL, bupropion, or to any of the inactive ingredients. See the end of this Medication Guide for a complete list of ingredients in FORFIVO XL.

What should I tell my healthcare provider before taking FORFIVO XL?
Tell your healthcare provider if you have ever had depression, suicidal thoughts or actions, or other mental health problems. You should also tell your healthcare provider about any symptoms you had during other times you tried to quit smoking, with or without bupropion. See “Quitting Smoking, Quit-Smoking Medications, Changes in Thinking and Behavior, Depression, and Suicidal Thoughts or Actions.”

- Tell your healthcare provider about your other medical conditions, including if you:
  - have liver problems, especially cirrhosis of the liver.
  - have kidney problems.
  - have, or have had, an eating disorder such as anorexia nervosa or bulimia.
  - have had a head injury.
  - have had a seizure (convulsion, fit).
  - have a tumor in your nervous system (brain or spine).
  - have had a heart attack, heart problems, or high blood pressure.
  - are a diabetic taking insulin or other medicines to control your blood sugar.
  - drink alcohol.
  - abuse prescription medicines or street drugs.
  - are pregnant or plan to become pregnant. Talk to your healthcare provider about the risk to your unborn baby if you take FORFIVO XL during pregnancy.
    - Tell your healthcare provider if you become pregnant or think you are pregnant during treatment with FORFIVO XL.
    - If you become pregnant during treatment with FORFIVO XL, talk to your healthcare provider about registering with the National Pregnancy Registry for Antidepressants. You can register by calling 1-844-405-6185.
  - are breastfeeding or plan to breastfeed during treatment with FORFIVO XL. FORFIVO XL passes into your milk. Talk to your healthcare provider about the best way to feed your baby during treatment with FORFIVO XL.

Tell your healthcare provider about all the medicines you take, including prescription, over-the-counter medicines, vitamins, and herbal supplements. Many medicines increase your chances of having seizures or other serious side effects if you take them while you are taking FORFIVO XL.

How should I take FORFIVO XL?

- Take FORFIVO XL exactly as prescribed by your healthcare provider. Do not change your dose or stop taking FORFIVO XL without talking with your healthcare provider first.
- Swallow FORFIVO XL tablets whole. Do not chew, cut, or crush FORFIVO XL tablets. If you do, the medicine will be released into your body too quickly. If this happens you may be more likely to get side effects including seizures. Tell your healthcare provider if you cannot swallow tablets.
- You may take FORFIVO XL with or without food.
- If you miss a dose, do not take an extra dose to make up for the dose you missed. Wait and take your next dose at the regular time. This is very important. Too much FORFIVO XL can increase your chance of having a seizure.
- If you take too much FORFIVO XL, or overdose, call your local emergency room or poison control center right away.
- Do not take any other medicines while taking FORFIVO XL unless your healthcare provider has told you it is okay.
- If you are taking FORFIVO XL for the treatment of major depressive disorder, it may take several weeks for you to feel that FORFIVO XL is working. Once you feel better, it is important to keep taking FORFIVO XL exactly as directed by your healthcare provider. Call your healthcare provider if you do not feel FORFIVO XL is working for you.

What should I avoid while taking FORFIVO XL?

- Avoid using alcohol during treatment with FORFIVO XL. If you usually drink a lot of alcohol, talk with your healthcare provider before suddenly stopping. If you suddenly stop drinking alcohol, you may increase your chance of having seizures.
- Do not drive a car or use heavy machinery until you know how FORFIVO XL affects you. FORFIVO XL can affect your ability to do these things safely.

What are possible side effects of FORFIVO XL?
FORFIVO XL can cause serious side effects. See the sections at the beginning of this Medication Guide for information about serious side effects of FORFIVO XL.
The most common side effects of FORFIVO XL include:

- trouble sleeping
- stuffy nose
- dry mouth
- dizziness
- feeling anxious
- nausea
- constipation
- joint aches

If you have nausea, take FORFIVO XL with food.
If you have trouble sleeping, do not take FORFIVO XL too close to bedtime.
Tell your healthcare provider right away about any side effects that bother you.
These are not all the possible side effects of FORFIVO XL. For more information, ask your healthcare provider or pharmacist.
Call your doctor for medical advice about side effects. You may report side effects to FDA at 1-800-FDA-1088.

How should I store FORFIVO XL?

- Store FORFIVO XL at room temperature between 68°F and 77°F (20°C to 25°C).

Keep FORFIVO XL and all medicines out of the reach of children.

General information about the safe and effective use of FORFIVO XL.
Medicines are sometimes prescribed for purposes other than those listed in a Medication Guide. Do not use FORFIVO XL for a condition for which it was not prescribed. Do not give FORFIVO XL to other people, even if they have the same symptoms you have. It may harm them.
If you take a urine drug screening test, FORFIVO XL may make the test result positive for amphetamines. If you tell the person giving you the drug screening test that you are taking FORFIVO XL, they can do a more specific drug screening test that should not have this problem.
This Medication Guide summarizes important information about FORFIVO XL. If you would like more information, talk with your healthcare provider. You can ask your healthcare provider or pharmacist for information about FORFIVO XL that is written for health professionals.
For more information about FORFIVO XL, call 1-844-518-2989.

What are the ingredients in FORFIVO XL?
Active ingredient: bupropion hydrochloride
Inactive ingredients: carboxymethyl cellulose sodium, colloidal silicon dioxide, hydrochloric acid, hydroxypropyl cellulose, hypromellose, magnesium stearate, methacrylic acid copolymer, polyethylene glycol 8000, polyethylene oxide, polyvinyl pyrrolidone and polyvinyl acetate blend, stearic acid, talc, titanium dioxide and triacetin. The tablets are printed with edible black ink.

FORFIVO XL is a registered trademark of TWi Pharmaceuticals Inc. All other product/brand names are trademarks of their
respective owners.

Manufactured by:
Pillar5 Pharma Inc.
Arnprior, Ontario K7S 0C9 Canada

Distributed by:
TWi Pharmaceuticals USA, Inc.
Paramus, NJ 07652

This Medication Guide has been approved by the U.S. Food and Drug Administration.

RL-IN000181 Revised: 11/2025

PACKAGE LABEL PRINCIPAL DISPLAY PANEL SECTION

NDC 24979-247-06

FORFIVO XL®

(bupropion hydrochloride extended-release tablets)

450 mg

Pharmacist: Dispense the accompanying Medication Guide to each patient

30 Tablets
Rx only